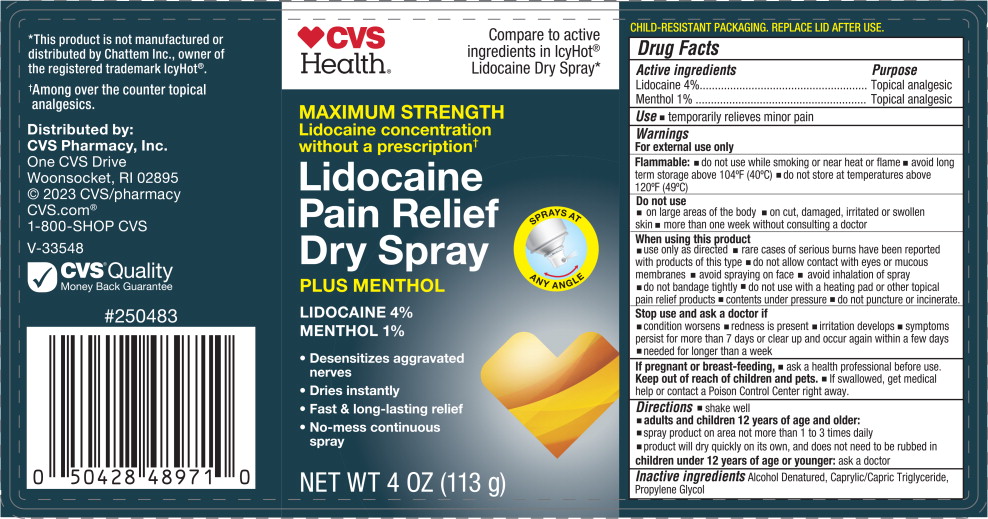 DRUG LABEL: CVS Cold and Hot Pain Relief Dry
NDC: 51316-483 | Form: SPRAY
Manufacturer: CVS Pharmacy
Category: otc | Type: HUMAN OTC DRUG LABEL
Date: 20260219

ACTIVE INGREDIENTS: LIDOCAINE 40 mg/1 g; MENTHOL, UNSPECIFIED FORM 10 mg/1 g
INACTIVE INGREDIENTS: ALCOHOL; PROPYLENE GLYCOL; CAPRYLIC/CAPRIC TRIGLYCERIDE

CVS Cold & Hot Pain Relief Dry Spray

Active ingredients

Lidocaine 4%

Menthol 1%

Purposes

Topical Analgesic

Topical Analgesic

Use

temporarily relieves minor pain

Warnings

For external use only

Flammable:

- do not use while smoking or near heat or flame
- avoid long term storage above 104°F (40°C)
- do not sore at temperatures above 120 °F (49°C)

Do not use

- on large areas of the body
- on cut, damaged, irritated or swollen skin
- more than one week without sonsulting a doctor

When using this product

- use only as directed
- rare cases of serious burns have been reported with products of this type
- do not allow contact with eyes or mucous membranes
- avoid spraying on face
- avoid inhalation of spray
- do not bandage tightly
- do not use with a heating pad or other topical pain relief products
- contents under pressure
- do not puncture or incinerate.

Stop use and ask a doctor if

- condition worsens
- redness is present
- irritation develops
- symptoms persist for more than 7 days or clear up and occur again within a few days
- needed for longer than a week

If pregnant or breast-feeding,

ask a health professional before use.

Keep out of reach of children.

If swallowed, get medical help or contact a Poison Control Center right away.

Directions

- shake well
- adults and children 12 years of age and older:
- spray product on area not more than 1 to 3 times daily
- product will dry quickly on its own, and does not need to be rubbed in
- children under 12 years of age: ask a doctor

Inactive ingredients

Alcohol Denatured, Caprylic/Capric Triglyceride, Propylene Glycol

Principal Display Panel - 113 g Can

CVS Health®

Compare to the active

ingredients in IcyHot®

Lidociane Dry Spray*

Maximum Strength

Lidocaine concentration

without a prescription†

Lidocaine

Pain Relief

Dry Spray

Plus Menthol

Sprays at any angle

Lidocaine 4%

Menthol 1%

- Desensitizes aggravated nerves
- Dries instantly
- Fast & long-lasting relief
- NO-mess continuous spray

NET WT 4 OZ (113 g)